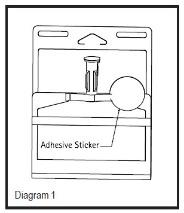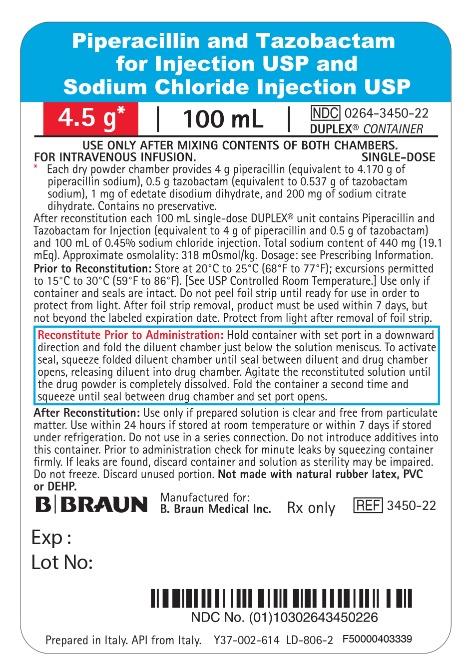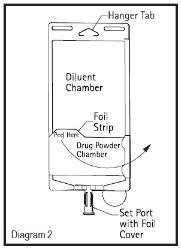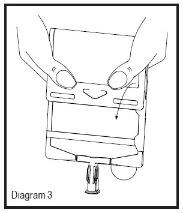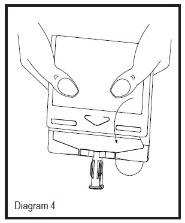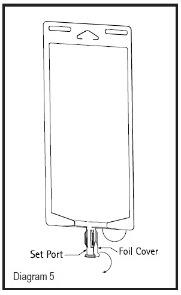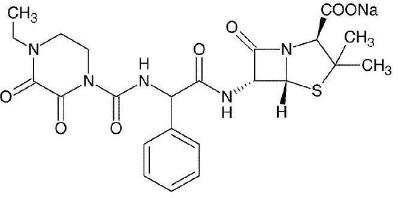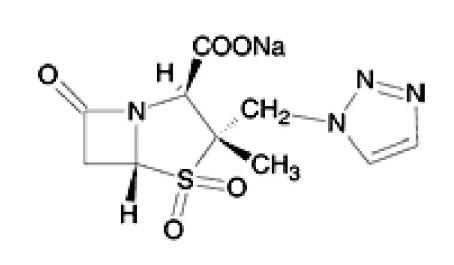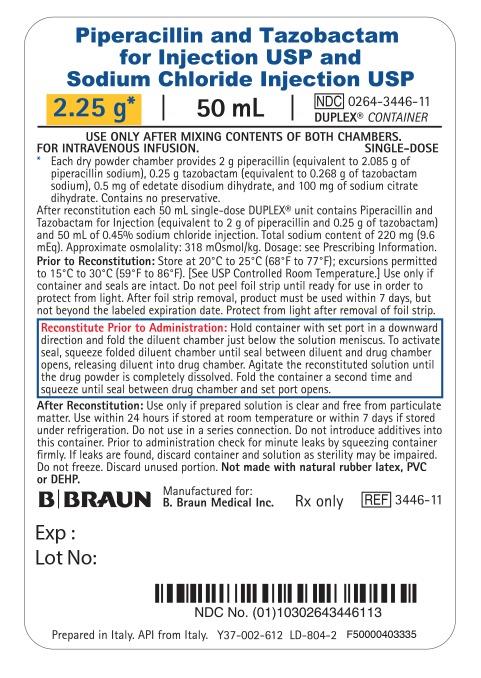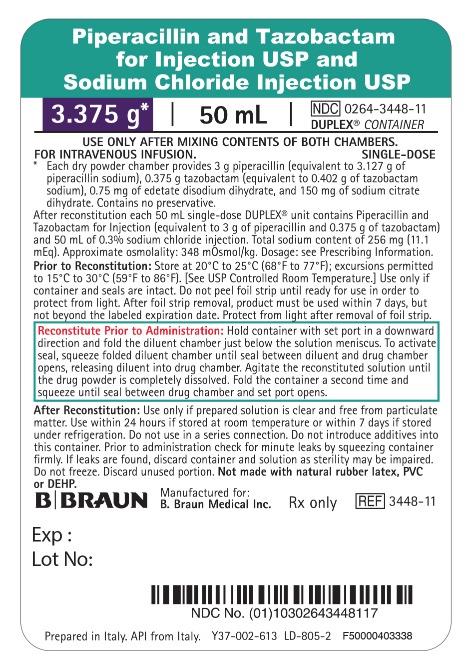 DRUG LABEL: Piperacillin and Tazobactam and Sodium Chloride
NDC: 0264-3446 | Form: INJECTION, SOLUTION
Manufacturer: B. Braun Medical Inc.
Category: prescription | Type: HUMAN PRESCRIPTION DRUG LABEL
Date: 20250417

ACTIVE INGREDIENTS: TAZOBACTAM SODIUM 250 mg/50 mL; PIPERACILLIN SODIUM 2 g/50 mL
INACTIVE INGREDIENTS: SODIUM CITRATE, UNSPECIFIED FORM 100 mg/50 mL; EDETATE DISODIUM 0.5 mg/50 mL; SODIUM CHLORIDE 225 mg/50 mL; WATER

HIGHLIGHTS OF PRESCRIBING INFORMATION

These highlights do not include all the information needed to use PIPERACILLIN AND TAZOBACTAM FOR INJECTION AND SODIUM CHLORIDE INJECTION safely and effectively. See full prescribing information for PIPERACILLIN AND TAZOBACTAM FOR INJECTION AND SODIUM CHLORIDE INJECTION.
PIPERACILLIN AND TAZOBACTAM for injection and SODIUM CHLORIDE injection, for intravenous use
Initial U.S. Approval: 1993

1 INDICATIONS AND USAGE

Piperacillin and Tazobactam for Injection and Sodium Chloride Injection, is a combination of piperacillin, a penicillin-class antibacterial and tazobactam, a beta-lactamase inhibitor, indicated for the treatment of:

- Intra-abdominal infections in adult and pediatric patients 2 months of age and older (1.1)
- Nosocomial pneumonia in adult and pediatric patients 2 months of age and older (1.2)
- Skin and skin structure infections in adults (1.3)
- Female pelvic infections in adults (1.4)
- Community-acquired pneumonia in adults (1.5)

Usage to Reduce Development of Drug-Resistant Bacteria

To reduce the development of drug-resistant bacteria and maintain the effectiveness of Piperacillin and Tazobactam for Injection and Sodium Chloride Injection and other antibacterial drugs, Piperacillin and Tazobactam for Injection and Sodium Chloride Injection should be used only to treat or prevent infections that are proven or strongly suspected to be caused by bacteria. (1.6)

2 DOSAGE AND ADMINISTRATION

- If a dose of Piperacillin and Tazobactam for Injection and Sodium Chloride injection is required that is not equal to 2.25 g, 3.375 g, or 4.5 g, this product is not recommended for use and an alternative formulation of piperacillin and tazobactam for injection should be considered (2.1).
- Adult Patients With Indications Other Than Nosocomial Pneumonia; The usual daily dosage of Piperacillin and Tazobactam for Injection and Sodium Chloride Injection, for intravenous use for adults is 3.375 g every 6 (six) hours. (2.2)
- Adult Patients with Nosocomial Pneumonia: Initial presumptive treatment of patients with nosocomial pneumonia should start with Piperacillin and Tazobactam for Injection and Sodium Chloride Injection, for intravenous use at a dosage of 4.5 g every 6 (six) hours plus an aminoglycoside. (2.3)
- Adult Patients with Renal Impairment: Dosage in patients with renal impairment (creatinine clearance ≤40 mL/min) and dialysis patients should be reduced, based on the degree of renal impairment. (2.4)
- Pediatric Patients by Indication and Age: See Table below (2.5)

Recommended Dosage of Piperacillin and Tazobactam for Injection and Sodium Chloride Injection for Pediatric Patients 2 months of Age and Older, Weighing up to 40 Kg and With Normal Renal Function
Age | Appendicitis and /or Peritonitis | Nosocomial Pneumonia
2 months to 9 months | 90 mg/kg (80 mg piperacillin and 10 mg tazobactam) every 8 (eight) hours | 90 mg/kg (80 mg piperacillin and 10 mg tazobactam) every 6 (six) hours
Older than 9 months | 112.5 mg/kg (100 mg piperacillin and 12.5 mg tazobactam) every 8 (eight) hours | 112.5 mg/kg (100 mg piperacillin and 12.5 mg tazobactam) every 6 (six) hours

- Administer Piperacillin and Tazobactam for Injection and Sodium Chloride Injection by intravenous infusion over 30 minutes to both adult and pediatric patients 2 months of age and older. (2.2, 2.3, 2.4, 2.5)
- Piperacillin and Tazobactam for Injection and Sodium Chloride Injection and aminoglycosides should be reconstituted and administered separately. Co-administration via Y-site can be done under certain conditions. (2.7)
- See the full prescribing information for the preparation and administration instructions for Piperacillin and Tazobactam for Injection and Sodium Chloride Injection single-dose DUPLEX® Container.

3 DOSAGE FORMS AND STRENGTHS

Piperacillin and Tazobactam for Injection and Sodium Chloride Injection in a single-dose DUPLEX® Container consisting of:

- 2.25 g Piperacillin and Tazobactam for Injection USP and 50 mL of 0.45% Sodium Chloride Injection USP (3)
- 3.375 g Piperacillin and Tazobactam for Injection USP and 50 mL of 0.3% Sodium Chloride Injection USP (3)
- 4.5 g Piperacillin and Tazobactam for Injection USP and 100 mL of 0.45% Sodium Chloride Injection USP (3)

4 CONTRAINDICATIONS

Patients with a history of allergic reactions to any of the penicillins, cephalosporins, or beta-lactamase inhibitors. (4)

5 WARNINGS AND PRECAUTIONS

- Serious hypersensitivity reactions (anaphylactic/anaphylactoid) reactions have been reported in patients receiving piperacillin and tazobactam. Discontinue Piperacillin and Tazobactam for Injection and Sodium Chloride Injection if a reaction occurs. (5.1)
- Piperacillin and tazobactam may cause severe cutaneous adverse reactions, such as Stevens-Johnson syndrome, toxic epidermal necrolysis, drug reaction with eosinophilia and systemic symptoms, and acute generalized exanthematous pustulosis. Discontinue Piperacillin and Tazobactam for Injection and Sodium Chloride Injection for progressive rashes. (5.2)
- Hemophagocytic lymphohistiocytosis (HLH) has been reported with the use of piperacillin and tazobactam. If HLH is suspected, discontinue Piperacillin and Tazobactam for Injection and Sodium Chloride Injection immediately. (5.3)
- Rhabdomyolysis: If signs or symptoms of rhabdomyolysis are observed, discontinue Piperacillin and Tazobactam for Injection and Sodium Chloride Injection and initiate appropriate therapy. (5.4)
- Hematological effects (including bleeding, leukopenia and neutropenia) have occurred. Monitor hematologic tests during prolonged therapy. (5.5)
- As with other penicillins, piperacillin and tazobactam may cause neuromuscular excitability or seizures. Patients receiving higher doses, especially in the presence of renal impairment may be at greater risk. Closely monitor patients with renal impairment or seizure disorders for signs and symptoms of neuromuscular excitability or seizures. (5.6)
- Nephrotoxicity in critically ill patients has been observed; the use of piperacillin and tazobactam was found to be an independent risk factor for renal failure and was associated with delayed recovery of renal function as compared to other beta-lactam antibacterial drugs in a randomized, multicenter, controlled trial in critically ill patients. Based on this study, alternative treatment options should be considered in the critically ill population. If alternative treatment options are inadequate or unavailable, monitor renal function during treatment with Piperacillin and Tazobactam for Injection and Sodium Chloride Injection. (5.7)
- High Sodium Load and Electrolyte Effects: Piperacillin and Tazobactam for Injection and Sodium Chloride Injection contains a total of 220 mg, 256 mg, 440 mg of sodium per 2.25 g, 3.375 g, and 4.5 g product, respectively. Consider an alternative formulation of piperacillin-tazobactam in patients requiring restricted sodium intake. Periodic electrolyte determinations should be performed in patients with low potassium reserves. (5.8)
- Clostridioides difficile-Associated Diarrhea: Evaluate patients if diarrhea occurs. (5.9)

6 ADVERSE REACTIONS

The most common adverse reactions (incidence >5%) are diarrhea, constipation, nausea, headache, and insomnia. (6.1)

To report SUSPECTED ADVERSE REACTIONS, contact B. Braun Medical Inc. at 1-833-425-1464 or FDA at 1-800-FDA-1088 or www.fda.gov/medwatch.

7 DRUG INTERACTIONS

- Piperacillin and Tazobactam for Injection and Sodium Chloride Injection administration can significantly reduce tobramycin concentrations in hemodialysis patients. Monitor tobramycin concentrations in these patients. (7.1)
- Probenecid prolongs the half-lives of piperacillin and tazobactam and should not be co-administered with Piperacillin and Tazobactam for Injection and Sodium Chloride Injection unless the benefit outweighs the risk. (7.2)
- Co-administration of Piperacillin and Tazobactam for Injection and Sodium Chloride Injection with vancomycin may increase the incidence of acute kidney injury. Monitor kidney function in patients receiving Piperacillin and Tazobactam for Injection and Sodium Chloride Injection and vancomycin. (7.3)
- Monitor coagulation parameters in patients receiving Piperacillin and Tazobactam for Injection and Sodium Chloride Injection and heparin or oral anticoagulants. (7.4)
- Piperacillin and Tazobactam for Injection and Sodium Chloride Injection may prolong the neuromuscular blockade of vecuronium and other non-depolarizing neuromuscular blockers. Monitor for adverse reactions related to neuromuscular blockade. (7.5)

8 USE IN SPECIFIC POPULATIONS

Dosage in patients with renal impairment (creatinine clearance ≤40 mL/min) should be reduced based on the degree of renal impairment. (2.4, 8.6)

FULL PRESCRIBING INFORMATION

1 INDICATIONS AND USAGE

1.1 Intra-abdominal Infections

Piperacillin and Tazobactam for Injection and Sodium Chloride Injection is indicated in adults and pediatric patients (2 months of age and older) for the treatment of appendicitis (complicated by rupture or abscess) and peritonitis caused by beta-lactamase producing isolates of Escherichia coli or the following members of the Bacteroides fragilis group: B. fragilis, B. ovatus, B. thetaiotaomicron, or B. vulgatus.

1.2 Nosocomial Pneumonia

Piperacillin and Tazobactam for Injection and Sodium Chloride Injection is indicated in adults and pediatric patients (2 months of age and older) for the treatment of nosocomial pneumonia (moderate to severe) caused by beta-lactamase producing isolates of Staphylococcus aureus and by piperacillin and tazobactam-susceptible Acinetobacter baumannii, Haemophilus influenzae, Klebsiella pneumoniae, and Pseudomonas aeruginosa (Nosocomial pneumonia caused by P. aeruginosa should be treated in combination with an aminoglycoside) [see Dosage and Administration (2)].

1.3 Skin and Skin Structure Infections

Piperacillin and Tazobactam for Injection and Sodium Chloride Injection is indicated in adults for the treatment of uncomplicated and complicated skin and skin structure infections, including cellulitis, cutaneous abscesses and ischemic/diabetic foot infections caused by beta-lactamase producing isolates of Staphylococcus aureus.

1.4 Female Pelvic Infections

Piperacillin and Tazobactam for Injection and Sodium Chloride Injection is indicated in adults for the treatment of postpartum endometritis or pelvic inflammatory disease caused by beta-lactamase producing isolates of Escherichia coli.

1.5 Community-acquired Pneumonia

Piperacillin and Tazobactam for Injection and Sodium Chloride Injection is indicated in adults for the treatment of community-acquired pneumonia (moderate severity only) caused by beta-lactamase producing isolates of Haemophilus influenzae.

1.6 Usage to Reduce Development of Drug-Resistant Bacteria

To reduce the development of drug-resistant bacteria and maintain the effectiveness of Piperacillin and Tazobactam for Injection and Sodium Chloride Injection and other antibacterial drugs, Piperacillin and Tazobactam for Injection and Sodium Chloride Injection should be used only to treat or prevent infections that are proven or strongly suspected to be caused by bacteria. When culture and susceptibility information are available, they should be considered in selecting or modifying antibacterial therapy. In the absence of such data, local epidemiology and susceptibility patterns may contribute to the empiric selection of therapy.

2 DOSAGE AND ADMINISTRATION

2.1 Important Administration Instructions

If a dose of Piperacillin and Tazobactam for Injection and Sodium Chloride Injection is required that does not equal 2.25 g, 3.375 g, or 4.5 g, this product is not recommended for use and an alternative formulation of piperacillin and tazobactam for injection should be considered.

2.2 Recommended Dosage in Adult Patients With Indications Other Than Nosocomial Pneumonia

The usual total daily dosage of Piperacillin and Tazobactam for Injection and Sodium Chloride Injection for adult patients with indications other than nosocomial pneumonia is 3.375 g every 6 (six) hours, to be administered by intravenous infusion over 30 minutes. The usual duration of Piperacillin and Tazobactam for Injection and Sodium Chloride Injection treatment is from 7 to 10 days.

2.3 Recommended Dosage in Adult Patients With Nosocomial Pneumonia

Initial presumptive treatment of adult patients with nosocomial pneumonia should start with Piperacillin and Tazobactam for Injection and Sodium Chloride Injection at a dosage of 4.5 g every 6 (six) hours plus an aminoglycoside, administered by intravenous infusion over 30 minutes. The recommended duration of Piperacillin and Tazobactam for Injection and Sodium Chloride Injection treatment for nosocomial pneumonia is 7 to 14 days. Treatment with the aminoglycoside should be continued in patients from whom P. aeruginosa is isolated.

2.4 Recommended Dosage in Adult Patients With Renal Impairment

In adult patients with renal impairment (creatinine clearance ≤ 40 mL/min) and dialysis patients (hemodialysis and CAPD), the intravenous dose of Piperacillin and Tazobactam for Injection and Sodium Chloride Injection should be reduced based on the degree of renal impairment. The recommended daily dosage of Piperacillin and Tazobactam for Injection and Sodium Chloride Injection for patients with renal impairment administered by intravenous infusion over 30 minutes is described in Table 1.

Table 1: Recommended Dosage of Piperacillin and Tazobactam in Patients with
Normal Renal Function and Renal Impairment
(As total grams piperacillin and tazobactam) [Administer Piperacillin and Tazobactam for Injection and Sodium Chloride Injection by intravenous infusion over 30 minutes.]
Creatinine clearance, mL/min | All Indications (except nosocomial pneumonia) | Nosocomial Pneumonia
Greater than 40 mL/min | 3.375 g every 6 hours | 4.5 g every 6 hours
20 to 40 mL/min [Creatinine clearance for patients not receiving hemodialysis] | 2.25 g every 6 hours | 3.375 g every 6 hours
Less than 20 mL/min | 2.25 g every 8 hours | 2.25 g every 6 hours
Hemodialysis [0.75 g (0.67 g piperacillin and 0.08 g tazobactam) should be administered following each hemodialysis session on hemodialysis days] | 2.25 g every 12 hours | 2.25 g every 8 hours
CAPD | 2.25 g every 12 hours | 2.25 g every 8 hours

For patients on hemodialysis, the maximum dose is 2.25 g every 12 hours for all indications other than nosocomial pneumonia and 2.25 g every 8 hours for nosocomial pneumonia. Since hemodialysis removes 30% to 40% of the administered dose, an additional dose of 0.75 g piperacillin and tazobactam for injection should be administered following each dialysis period on hemodialysis days. No additional dosage of Piperacillin and Tazobactam for Injection and Sodium Chloride Injection is necessary for CAPD patients.

2.5 Dosage in Pediatric Patients 2 months of Age and Older With Appendicitis (complicated by rupture or abscess) and/or Peritonitis or Nosocomial Pneumonia with normal renal function

If a dose of Piperacillin and Tazobactam for Injection and Sodium Chloride injection is required that is not equal to 2.25 g, 3.375 g, or 4.5 g, this product is not recommended for use and an alternative formulation of piperacillin and tazobactam for injection should be considered [see Use in Specific Populations (8.4)].

The recommended dosage for pediatric patients with appendicitis (complicated by rupture or abscess) and/or peritonitis or nosocomial pneumonia aged 2 months of age and older, weighing up to 40 kg, and with normal renal function, is described in Table 2 [see Use in Specific Populations (8.4) and Clinical Pharmacology (12.3)].

Table 2: Recommended Dosage of Piperacillin and Tazobactam in Pediatric Patients
2 Months of Age and Older, Weighing Up to 40 kg, and With Normal Renal Function [Administer Piperacillin and Tazobactam for Injection and Sodium Chloride Injection by intravenous infusion over 30 minutes]
Age | Appendicitis and/or Peritonitis | Nosocomial Pneumonia
2 months to 9 months | 90 mg/kg (80 mg piperacillin and 10 mg tazobactam) every 8 (eight) hours | 90 mg/kg (80 mg piperacillin and 10 mg tazobactam) every 6 (six) hours
Older than 9 months of age | 112.5 mg/kg (100 mg piperacillin and 12.5 mg tazobactam) every 8 (eight) hours | 112.5 mg/kg (100 mg piperacillin and 12.5 mg tazobactam) every 6 (six) hours

Pediatric patients weighing over 40 kg and with normal renal function should receive the adult dose [see Dosage and Administration (2.2, 2.3)].

Dosage of Piperacillin and Tazobactam for Injection and Sodium Chloride Injection in pediatric patients with renal impairment has not been determined.

2.6 Preparation and Administration of Piperacillin and Tazobactam for Injection and Sodium Chloride Injection in the DUPLEX® Container

Important Administration Instructions

- Do not use in series connections. Such use would result in air embolism due to residual air being drawn from the primary container before administration of the fluid from the secondary container is complete. If administration is controlled by a pumping device, care must be taken to discontinue pumping action before the container runs dry or air embolism may result.
- Do not introduce additives into the DUPLEX® Container.
- Piperacillin and Tazobactam for Injection and Sodium Chloride Injection is not chemically stable in solutions that contain only sodium bicarbonate and solutions that significantly alter the pH.
- Piperacillin and Tazobactam for Injection and Sodium Chloride Injection should not be added to blood products or albumin hydrolysates.
- Parenteral drug products should be inspected visually for particulate matter and discoloration prior to administration, whenever solution and container permit.
- Use only if solution is clear and container and seals are intact.
- Administer Piperacillin and Tazobactam for Injection and Sodium Chloride Injection intravenously over 30 minutes.
- This reconstituted solution is for intravenous use only.

DUPLEX® Container Storage

- To avoid inadvertent activation, the DUPLEX® Container should remain in the folded position
  until activation is intended.

Patient Labeling and Drug Powder/Diluent Inspection

- Apply patient-specific label on foil side of container. Use care to avoid activation. Do not cover any portion of foil strip with patient label.
- Peel sticker halfway off and unfold DUPLEX® Container (see Diagram 1).
- Visually inspect diluent chamber for particulate matter.
- Use only if container and seals are intact.
- To inspect the drug powder for foreign matter or discoloration, peel foil strip from drug chamber (see Diagram 2).

- Protect from light after removal of foil strip.
  Note: If foil strip is removed, the container should be re-folded and the sticker reapplied until ready to activate. The product must then be used within 7 days at room temperature at 20°C to 25°C (68°F to 77°F), but not beyond the labeled expiration date.

Reconstitution (Activation)

- Do not use directly after storage by refrigeration, allow the product to equilibrate to room temperature before patient use.
- Unfold the DUPLEX® Container and point the set port in a downward direction. Starting at the hanger tab end, fold the DUPLEX® Container just below the diluent meniscus trapping all air above the fold. To activate, squeeze the folded diluent chamber until the seal between the diluent and powder opens, releasing diluent into the drug powder chamber (see Diagram 3).
- Agitate the liquid-powder mixture until the drug powder is completely dissolved.
  Note: Following reconstitution (activation), the reconstituted product must be used within 24 hours if stored at room temperature at 20°C to 25°C (68°F to 77°F) or within 7 days if stored under refrigeration at 2°C to 8°C (36°F to 46°F).

Administration

- Visually inspect the reconstituted solution for particulate matter.
- Point the set port in a downwards direction. Starting at the hanger tab end, fold the DUPLEX® Container just below the solution meniscus trapping all air above the fold. Squeeze the folded DUPLEX® Container until the seal between reconstituted drug solution and set port opens, releasing liquid to set port (see Diagram 4).
- Prior to attaching the intravenous set, check for minute leaks by squeezing container firmly. If leaks are found, discard container and solution as sterility may be compromised.
- Using aseptic technique, peel foil cover from the set port and attach sterile administration set (see Diagram 5).
- Refer to directions for use accompanying the administration set.
- Discard unused portion.

Compatible Intravenous Solutions for Co-administration via a Y-site

0.9% sodium chloride for injection
Sterile water for injection (Maximum recommended volume per dose of sterile water for injection is 50 mL)

Dextrose 5%
Lactated Ringer's Solution

Piperacillin and Tazobactam for Injection and Sodium Chloride Injection should not be mixed with other drugs in a syringe or infusion bottle since compatibility has not been established.

Piperacillin and Tazobactam for Injection and Sodium Chloride Injection for Pediatric Patients Weighing up to 40 kg

The volume of reconstituted solution required to deliver the dose of Piperacillin and Tazobactam is dependent on the weight of the pediatric patient [see Dosage and Administration (2.5)].

1. Calculate patient dose as described in Table 2 above [see Dosage and Administration (2.5)].
2. Piperacillin and Tazobactam for Injection and Sodium Chloride Injection in the DUPLEX® Container should be used only in patients who require the entire 2.25 g, 3.375 g, or 4.5 g dose and not any fraction thereof.

Stability of Piperacillin and Tazobactam for Injection and Sodium Chloride Injection Following Reconstitution

Stability studies after reconstitution in the DUPLEX® Containers, have demonstrated chemical stability (potency, pH of reconstituted solution and clarity of solution) for up to 24 hours at room temperature at 20°C to 25°C (68°F to 77°F) and up to 7 days at refrigerated temperature at 2°C to 8°C (36°F to 46°F). Piperacillin and Tazobactam for Injection and Sodium Chloride Injection contains no preservatives. Appropriate consideration of aseptic technique should be used.

2.7 Compatibility With Aminoglycosides

Due to the in vitro inactivation of aminoglycosides by piperacillin, Piperacillin and Tazobactam for Injection and Sodium Chloride Injection and aminoglycosides are recommended for separate administration. Piperacillin and Tazobactam for Injection and Sodium Chloride Injection and aminoglycosides should be reconstituted and administered separately when concomitant therapy with aminoglycosides is indicated [see Drug Interactions (7.1)].

In circumstances where co-administration via Y-site is necessary, Piperacillin and Tazobactam for Injection and Sodium Chloride Injection is compatible for simultaneous co-administration via Y-site infusion only with the following aminoglycosides under the following conditions:

Table 3: Compatibility with Aminoglycosides
Aminoglycoside | Piperacillin and Tazobactam Dose | Piperacillin and Tazobactam Diluent Volume | Aminoglycoside Concentration Range [The concentration ranges in Table 3 are based on administration of the aminoglycoside in divided doses (10 to 15 mg/kg/day in two daily doses for amikacin and 3 to 5 mg/kg/day in three daily doses for gentamicin). Administration of amikacin or gentamicin in a single daily dose or in doses exceeding those stated above via Y-site with Piperacillin and Tazobactam for Injection and Sodium Chloride Injection has not been evaluated. See package insert for each aminoglycoside for complete Dosage and Administration instructions.] | Acceptable Diluents for Aminoglycosides
Amikacin | 2.25 g; 3.375 g; 4.5 g | 50 mL; 50 mL; 100 mL | 1.75 mg/mL to 7.5 mg/mL | 0.9% sodium chloride or 5% dextrose
Gentamicin | 2.25 g; 3.375 g; 4.5 g | 50 mL; 50 mL; 100 mL | 0.7 mg/mL to 3.32 mg/mL | 0.9% sodium chloride or 5% dextrose

Only the concentration and diluents for amikacin or gentamicin with the dosages of Piperacillin and Tazobactam for Injection and Sodium Chloride Injection listed above have been established as compatible for co-administration via Y-site infusion. Simultaneous co-administration via Y-site infusion in any manner other than listed above may result in inactivation of the aminoglycoside by Piperacillin and Tazobactam for Injection and Sodium Chloride Injection.

Piperacillin and Tazobactam for Injection and Sodium Chloride Injection is not compatible with tobramycin for simultaneous co-administration via Y-site infusion. Compatibility of Piperacillin and Tazobactam for Injection and Sodium Chloride Injection with other aminoglycosides has not been established.

3 DOSAGE FORMS AND STRENGTHS

Piperacillin and Tazobactam for Injection USP and Sodium Chloride Injection USP is supplied as a white to off-white powder and a clear, colorless solution in a single-dose DUPLEX® Container consisting of:

- 2.25 g Piperacillin and Tazobactam for Injection USP (2 g of piperacillin and 0.25 g of tazobactam) and 50 mL of 0.45% Sodium Chloride Injection USP.
- 3.375 g Piperacillin and Tazobactam for Injection USP (3 g of piperacillin and 0.375 g of tazobactam) and 50 mL of 0.3% Sodium Chloride Injection USP.
- 4.5 g Piperacillin and Tazobactam for Injection USP (4 g of piperacillin and 0.5 g of tazobactam) and 100 mL of 0.45% Sodium Chloride Injection USP.

4 CONTRAINDICATIONS

Piperacillin and Tazobactam for Injection and Sodium Chloride Injection is contraindicated in patients with a history of allergic reactions to any of the penicillins, cephalosporins, or betalactamase inhibitors.

5 WARNINGS AND PRECAUTIONS

5.1 Hypersensitivity Adverse Reactions

Serious and occasionally fatal hypersensitivity (anaphylactic/anaphylactoid) reactions (including shock) have been reported in patients receiving therapy with piperacillin and tazobactam. These reactions are more likely to occur in individuals with a history of penicillin, cephalosporin, or carbapenem hypersensitivity or a history of sensitivity to multiple allergens. Before initiating therapy with Piperacillin and Tazobactam for Injection and Sodium Chloride Injection, careful inquiry should be made concerning previous hypersensitivity reactions. If an allergic reaction occurs, Piperacillin and Tazobactam for Injection and Sodium Chloride Injection should be discontinued and appropriate therapy instituted.

5.2 Severe Cutaneous Adverse Reactions

Piperacillin and tazobactam may cause severe cutaneous adverse reactions, such as Stevens-Johnson syndrome, toxic epidermal necrolysis, drug reaction with eosinophilia and systemic symptoms, and acute generalized exanthematous pustulosis. If patients develop a skin rash they should be monitored closely and Piperacillin and Tazobactam for Injection and Sodium Chloride Injection discontinued if lesions progress.

5.3 Hemophagocytic Lymphohistiocytosis

Cases of hemophagocytic lymphohistiocytosis (HLH) have been reported in pediatric and adult patients treated with piperacillin and tazobactam. Signs and symptoms of HLH may include fever, rash, lymphadenopathy, hepatosplenomegaly and cytopenia. If HLH is suspected, discontinue Piperacillin and Tazobactam for Injection and Sodium Chloride Injection immediately and institute appropriate management.

5.4 Rhabdomyolysis

Rhabdomyolysis has been reported with the use of piperacillin and tazobactam [see Adverse Reactions (6.2)]. If signs or symptoms of rhabdomyolysis such as muscle pain, tenderness or weakness, dark urine, or elevated creatine phosphokinase are observed, discontinue Piperacillin and Tazobactam for Injection and Sodium Chloride Injection and initiate appropriate therapy.

5.5 Hematologic Adverse Reactions

Bleeding manifestations have occurred in some patients receiving beta-lactam drugs, including piperacillin. These reactions have sometimes been associated with abnormalities of coagulation tests such as clotting time, platelet aggregation and prothrombin time, and are more likely to occur in patients with renal failure. If bleeding manifestations occur, Piperacillin and Tazobactam for Injection and Sodium Chloride Injection should be discontinued, and appropriate therapy instituted.

The leukopenia/neutropenia associated with piperacillin and tazobactam administration appears to be reversible and most frequently associated with prolonged administration.

Periodic assessment of hematopoietic function should be performed, especially with prolonged therapy, i.e., ≥ 21 days [see Adverse Reactions (6.1)].

5.6 Central Nervous System Adverse Reactions

As with other penicillins, piperacillin and tazobactam may cause neuromuscular excitability or seizures. Patients receiving higher doses, especially patients with renal impairment may be at greater risk for central nervous system adverse reactions. Closely monitor patients with renal impairment or seizure disorders for signs and symptoms of neuromuscular excitability or seizures [see Adverse Reactions (6.2)].

5.7 Nephrotoxicity in Critically Ill Patients

The use of piperacillin and tazobactam was found to be an independent risk factor for renal failure and was associated with delayed recovery of renal function as compared to other beta-lactam antibacterial drugs in a randomized, multicenter, controlled trial in critically ill patients [see Adverse Reactions (6.1)]. Based on this study, alternative treatment options should be considered in the critically ill population. If alternative treatment options are inadequate or unavailable, monitor renal function during treatment with Piperacillin and Tazobactam for Injection and Sodium Chloride Injection [see Dosage and Administration (2.4)].

Combined use of piperacillin and tazobactam and vancomycin may be associated with an increased incidence of acute kidney injury [see Drug Interactions (7.3)].

5.8 High Sodium Load and Electrolyte Effects

Piperacillin and Tazobactam for Injection and Sodium Chloride Injection contains a total of 220 mg, 256 mg, and 440 mg of sodium per 2.25 g, 3.375 g, and 4.5 g product, respectively. Consider using an alternative formulation of piperacillin and tazobactam when treating patients requiring restricted salt intake. Periodic electrolyte determinations should be performed in patients with low potassium reserves, and the possibility of hypokalemia should be kept in mind with patients who have potentially low potassium reserves and who are receiving cytotoxic therapy or diuretics.

5.9 Clostridioides difficile-Associated Diarrhea

Clostridioides difficile-associated diarrhea (CDAD) has been reported with use of nearly all antibacterial agents, including piperacillin and tazobactam, and may range in severity from mild diarrhea to fatal colitis. Treatment with antibacterial agents alters the normal flora of the colon leading to overgrowth of C. difficile.

C. difficile produces toxins A and B which contribute to the development of CDAD. Hypertoxin producing strains of C. difficile cause increased morbidity and mortality, as these infections can be refractory to antimicrobial therapy and may require colectomy. CDAD must be considered in all patients who present with diarrhea following antibacterial drug use. Careful medical history is necessary since CDAD has been reported to occur over two months after the administration of antibacterial agents.

If CDAD is suspected or confirmed, ongoing antibacterial drug use not directed against C. difficile may need to be discontinued. Appropriate fluid and electrolyte management, protein supplementation, antibacterial treatment of C. difficile, and surgical evaluation should be instituted as clinically indicated.

5.10 Development of Drug-Resistant Bacteria

Prescribing Piperacillin and Tazobactam for Injection and Sodium Chloride Injection in the absence of a proven or strongly suspected bacterial infection or a prophylactic indication is unlikely to provide benefit to the patient and increases the risk of development of drug-resistant bacteria.

6 ADVERSE REACTIONS

The following clinically significant adverse reactions are described elsewhere in the labeling:

- Hypersensitivity Adverse Reactions [see Warnings and Precautions (5.1)]
- Severe Cutaneous Adverse Reactions [see Warnings and Precautions (5.2)]
- Hemophagocytic Lymphohistiocytosis [see Warnings and Precautions (5.3)]
- Rhabdomyolysis [see Warnings and Precautions (5.4)]
- Hematologic Adverse Reactions [see Warnings and Precautions (5.5)]
- Central Nervous System Adverse Reactions [see Warnings and Precautions (5.6)]
- Nephrotoxicity in Critically Ill Patients [see Warnings and Precautions (5.7)]
- High Sodium Load and Electrolyte Effects [see Warnings and Precautions (5.8)]
- Clostridioides difficile-Associated Diarrhea [see Warnings and Precautions (5.9)]

6.1 Clinical Trials Experience

Because clinical trials are conducted under widely varying conditions, adverse reaction rates observed in the clinical trials of a drug cannot be directly compared to rates in the clinical trials of another drug and may not reflect the rates observed in practice.

The safety of Piperacillin and Tazobactam for Injection and Sodium Chloride Injection has been established from adequate and well-controlled studies of piperacillin and tazobactam. Below is a display of the adverse reactions of piperacillin and tazobactam in these adequate and well controlled studies.

Clinical Trials in Adult Patients

During the initial clinical investigations, 2621 patients worldwide were treated with piperacillin and tazobactam in phase 3 trials. In the key North American monotherapy clinical trials (n=830 patients), 90% of the adverse events reported were mild to moderate in severity and transient in nature. However, in 3.2% of the patients treated worldwide, piperacillin and tazobactam was discontinued because of adverse events primarily involving the skin (1.3%), including rash and pruritus; the gastrointestinal system (0.9%), including diarrhea, nausea, and vomiting; and allergic reactions (0.5%).

Table 4: Adverse Reactions from Piperacillin and Tazobactam Monotherapy Clinical Trials

System Organ Class
Adverse Reaction

Gastrointestinal disorders

Diarrhea (11.3%)

Constipation (7.7%)

Nausea (6.9%)

Vomiting (3.3%)

Dyspepsia (3.3%)

Abdominal pain (1.3%)

General disorders and administration site conditions

Fever (2.4%)

Injection site reaction (≤1%)

Rigors (≤1%)

Immune system disorders

Anaphylaxis (≤1%)

Infections and infestations

Candidiasis (1.6%)

Pseudomembranous colitis (≤1%)

Metabolism and nutrition disorders

Hypoglycemia (≤1%)

Musculoskeletal and connective tissue disorders

Myalgia (≤1%)

Arthralgia (≤1%)

Nervous system disorders

Headache (7.7%)

Psychiatric disorders

Insomnia (6.6%)

Skin and subcutaneous tissue disorders

Rash (4.2%, including maculopapular, bullous, and urticarial)

Pruritus (3.1%)

Purpura (≤1%)

Vascular disorders

Phlebitis (1.3%)

Thrombophlebitis (≤1%)

Hypotension (≤1%)

Flushing (≤1%)

Respiratory, thoracic and mediastinal disorders

Epistaxis (≤1%)

Nosocomial Pneumonia Trials

Two trials of nosocomial lower respiratory tract infections were conducted. In one study, 222 patients were treated with piperacillin and tazobactam in a dosing regimen of 4.5 g every 6 hours in combination with an aminoglycoside and 215 patients were treated with imipenem/cilastatin (500 mg/500 mg every 6 hours) in combination with an aminoglycoside. In this trial, treatment-emergent adverse events were reported by 402 patients, 204 (91.9%) in the piperacillin and tazobactam group and 198 (92.1%) in the imipenem/cilastatin group. Twenty-five (11.0%) patients in the piperacillin and tazobactam group and 14 (6.5%) in the imipenem/cilastatin group (p > 0.05) discontinued treatment due to an adverse event.

The second trial used a dosing regimen of 3.375 g given every 4 hours with an aminoglycoside.

Table 5: Adverse Reactions from Piperacillin and Tazobactam
Plus Aminoglycoside Clinical Trials [For adverse drug reactions that appeared in both studies the higher frequency is presented.]

System Organ Class
Adverse Reaction

Blood and lymphatic system disorders

Thrombocythemia (1.4%)

Anemia (≤1%)

Thrombocytopenia (≤1%)

Eosinophilia (≤1%)

Gastrointestinal disorders

Diarrhea (20%)

Constipation (8.4%)

Nausea (5.8%)

Vomiting (2.7%)

Dyspepsia (1.9%)

Abdominal pain (1.8%)

Stomatitis (≤1%)

General disorders and administration site conditions

Fever (3.2%)

Injection site reaction (≤1%)

Infections and infestations

Oral candidiasis (3.9%)

Candidiasis (1.8%)

Investigations

BUN increased (1.8%)

Blood creatinine increased (1.8%)

Liver function test abnormal (1.4%)

Alkaline phosphatase increased (≤1%)

Aspartate aminotransferase increased (≤1%)

Alanine aminotransferase increased (≤1%)

Metabolism and nutrition disorders

Hypoglycemia (≤1%)

Hypokalemia (≤1%)

Nervous system disorders

Headache (4.5%)

Psychiatric disorders

Insomnia (4.5%)

Renal and urinary disorders

Renal failure (≤1%)

Skin and subcutaneous tissue disorders

Rash (3.9%)

Pruritus (3.2%)

Vascular disorders

Thrombophlebitis (1.3%)

Hypotension (1.3%)

Other Trials: Nephrotoxicity

In a randomized, multicenter, controlled trial in 1200 adult critically ill patients, piperacillin and tazobactam was found to be a risk factor for renal failure (odds ratio 1.7, 95% CI 1.18 to 2.43), and associated with delayed recovery of renal function as compared to other beta-lactam antibacterial drugs^1 [see Warnings and Precautions (5.7)].

Adverse Laboratory Changes (Seen During Clinical Trials)

Of the trials reported, including that of nosocomial lower respiratory tract infections in which a higher dose of piperacillin and tazobactam was used in combination with an aminoglycoside, changes in laboratory parameters include:

Hematologic—decreases in hemoglobin and hematocrit, thrombocytopenia, increases in platelet count, eosinophilia, leukopenia, neutropenia. These patients were withdrawn from therapy; some had accompanying systemic symptoms (e.g., fever, rigors, chills)

Coagulation—positive direct Coombs' test, prolonged prothrombin time, prolonged partial thromboplastin time

Hepatic—transient elevations of AST (SGOT), ALT (SGPT), alkaline phosphatase, bilirubin

Renal—increases in serum creatinine, blood urea nitrogen

Additional laboratory events include abnormalities in electrolytes (i.e., increases and decreases in sodium, potassium, and calcium), hyperglycemia, decreases in total protein or albumin, blood glucose decreased, gamma-glutamyltransferase increased, hypokalemia, and bleeding time prolonged.

Clinical Trials in Pediatric Patients

Clinical studies of piperacillin and tazobactam in pediatric patients suggest a similar safety profile to that seen in adults.

In a prospective, randomized, comparative, open-label clinical trial of pediatric patients, 2 to 12 years of age, with intra-abdominal infections (including appendicitis and/or peritonitis), 273 patients were treated with piperacillin and tazobactam 112.5 mg/kg given intravenously every 8 hours and 269 patients were treated with cefotaxime (50 mg/kg) plus metronidazole (7.5 mg/kg) every 8 hours. In this trial, adverse reactions were reported by 146 patients, 73 (26.7%) in the piperacillin and tazobactam group and 73 (27.1%) in the cefotaxime/metronidazole group. Six patients (2.2%) in the piperacillin and tazobactam group and 5 patients (1.9%) in the cefotaxime/metronidazole group discontinued due to an adverse event.

In a retrospective, cohort study, 140 pediatric patients 2 months to less than 18 years of age with nosocomial pneumonia were treated with piperacillin and tazobactam and 267 patients were treated with comparators (which included ticarcillin-clavulanate, carbapenems, ceftazidime, cefepime, or ciprofloxacin). The rates of serious adverse reactions were generally similar between the piperacillin and tazobactam and comparator groups, including patients aged 2 months to 9 months treated with piperacillin and tazobactam 90 mg/kg intravenously every 6 hours and patients older than 9 months and less than 18 years of age treated with piperacillin and tazobactam 112.5 mg/kg intravenously every 6 hours.

6.2 Postmarketing Experience

In addition to the adverse drug reactions identified in clinical trials in Table 4 and Table 5, the following adverse reactions have been identified during post-approval use of piperacillin and tazobactam. Because these reactions are reported voluntarily from a population of uncertain size, it is not always possible to reliably estimate their frequency or establish a causal relationship to drug exposure.

Hepatobiliary—hepatitis, jaundice

Hematologic—hemolytic anemia, agranulocytosis, pancytopenia

Immune—hypersensitivity reactions, anaphylactic/anaphylactoid reactions (including shock), hemophagocytic lymphohistiocytosis (HLH), acute myocardial ischemia with or without myocardial infarction may occur as part of an allergic reaction

Renal—interstitial nephritis

Nervous system disorders—seizures

Psychiatric disorders—delirium

Respiratory—eosinophilic pneumonia

Skin and Appendages—erythema multiforme, Stevens-Johnson syndrome, toxic epidermal necrolysis, drug reaction with eosinophilia and systemic symptoms, (DRESS), acute generalized exanthematous pustulosis (AGEP), dermatitis exfoliative, and linear IgA bullous dermatosis

Musculoskeletal—rhabdomyolysis

Postmarketing experience with piperacillin and tazobactam in pediatric patients suggests a similar safety profile to that seen in adults.

6.3 Additional Experience with Piperacillin

The following adverse reaction has also been reported for piperacillin for injection:

Skeletal—prolonged neuromuscular blockade [see Drug Interactions (7.5)].

7 DRUG INTERACTIONS

7.1 Aminoglycosides

Piperacillin may inactivate aminoglycosides by converting them to microbiologically inert amides.

In vivo inactivation:

When aminoglycosides are administered in conjunction with piperacillin to patients with end-stage renal disease requiring hemodialysis, the concentrations of the aminoglycosides (especially tobramycin) may be significantly reduced and should be monitored.

Sequential administration of piperacillin and tazobactam and tobramycin to patients with either normal renal function or mild to moderate renal impairment has been shown to modestly decrease serum concentrations of tobramycin but no dosage adjustment is considered necessary.

In vitro inactivation:

Due to the in vitro inactivation of aminoglycosides by piperacillin, piperacillin and tazobactam and aminoglycosides are recommended for separate administration. Piperacillin and Tazobactam for Injection and Sodium Chloride Injection and aminoglycosides should be reconstituted, and administered separately when concomitant therapy with aminoglycosides is indicated. Piperacillin and Tazobactam for Injection and Sodium Chloride Injection, which contains EDTA, is compatible with amikacin and gentamicin for simultaneous Y-site infusion in certain diluents and at specific concentrations. Piperacillin and Tazobactam for Injection and Sodium Chloride Injection is not compatible with tobramycin for simultaneous Y-site infusion [see Dosage and Administration (2.7)].

7.2 Probenecid

Probenecid administered concomitantly with Piperacillin and Tazobactam for Injection and Sodium Chloride Injection prolongs the half-life of piperacillin by 21% and that of tazobactam by 71% because probenecid inhibits tubular renal secretion of both piperacillin and tazobactam. Probenecid should not be co-administered with Piperacillin and Tazobactam for Injection and Sodium Chloride Injection unless the benefit outweighs the risk.

7.3 Vancomycin

Studies have detected an increased incidence of acute kidney injury in patients concomitantly administered piperacillin and tazobactam and vancomycin as compared to vancomycin alone [see Warnings and Precautions (5.7)].

Monitor kidney function in patients concomitantly administered with Piperacillin and Tazobactam for Injection and Sodium Chloride Injection and vancomycin.

No pharmacokinetic interactions have been noted between piperacillin and tazobactam and vancomycin.

7.4 Anticoagulants

Coagulation parameters should be tested more frequently and monitored regularly during simultaneous administration of high doses of heparin, oral anticoagulants, or other drugs that may affect the blood coagulation system or the thrombocyte function [see Warnings and Precautions (5.5)].

7.5 Vecuronium

Piperacillin when used concomitantly with vecuronium has been implicated in the prolongation of the neuromuscular blockade of vecuronium. Piperacillin and Tazobactam for Injection and Sodium Chloride Injection could produce the same phenomenon if given along with vecuronium. Due to their similar mechanism of action, it is expected that the neuromuscular blockade produced by any of the non-depolarizing neuromuscular blockers could be prolonged in the presence of piperacillin. Monitor for adverse reactions related to neuromuscular blockade (see package insert for vecuronium bromide).

7.6 Methotrexate

Limited data suggests that co-administration of methotrexate and piperacillin may reduce the clearance of methotrexate due to competition for renal secretion. The impact of tazobactam on the elimination of methotrexate has not been evaluated. If concurrent therapy is necessary, serum concentrations of methotrexate as well as the signs and symptoms of methotrexate toxicity should be frequently monitored.

7.7 Effects on Laboratory Tests

There have been reports of positive test results using the Bio-Rad Laboratories Platelia Aspergillus EIA test in patients receiving piperacillin and tazobactam injection who were subsequently found to be free of Aspergillus infection. Cross-reactions with non-Aspergillus polysaccharides and polyfuranoses with the Bio-Rad Laboratories Platelia Aspergillus EIA test have been reported. Therefore, positive test results in patients receiving piperacillin and tazobactam should be interpreted cautiously and confirmed by other diagnostic methods.

As with other penicillins, the administration of piperacillin and tazobactam may result in a false-positive reaction for glucose in the urine using a copper-reduction method (CLINITEST®). It is recommended that glucose tests based on enzymatic glucose oxidase reactions be used.

8 USE IN SPECIFIC POPULATIONS

8.1 Pregnancy

Risk Summary

Piperacillin and tazobactam cross the placenta in humans. However, there are insufficient data with piperacillin and/or tazobactam in pregnant women to inform a drug-associated risk for major birth defects and miscarriage. No fetal structural abnormalities were observed in rats or mice when piperacillin and tazobactam was administered intravenously during organogenesis at doses 1 to 2 times and 2 to 3 times the human dose of piperacillin and tazobactam, respectively, based on body-surface area (mg/m^2). However, fetotoxicity in the presence of maternal toxicity was observed in developmental toxicity and peri/postnatal studies conducted in rats (intraperitoneal administration prior to mating and throughout gestation or from gestation day 17 through lactation day 21) at doses less than the maximum recommended human daily dose based on body-surface area (mg/m^2) (see Data).

The background risk of major birth defects and miscarriage for the indicated population is unknown. In the U.S. general population, the estimated background risk of major birth defects and miscarriage in clinically recognized pregnancies is 2 to 4% and 15 to 20%, respectively.

Data

Animal Data

In embryo-fetal development studies in mice and rats, pregnant animals received intravenous doses of piperacillin and tazobactam up to 3000/750 mg/kg/day during the period of organogenesis. There was no evidence of teratogenicity up to the highest dose evaluated, which is 1 to 2 times and 2 to 3 times the human dose of piperacillin and tazobactam, in mice and rats respectively, based on body-surface area (mg/m^2). Fetal body weights were reduced in rats at maternally toxic doses at or above 500/62.5 mg/kg/day, minimally representing 0.4 times the human dose of both piperacillin and tazobactam based on body-surface area (mg/m^2).

A fertility and general reproduction study in rats using intraperitoneal administration of tazobactam or the combination piperacillin and tazobactam prior to mating and through the end of gestation, reported a decrease in litter size in the presence of maternal toxicity at 640 mg/kg/day tazobactam (4 times the human dose of tazobactam based on body-surface area), and decreased litter size and an increase in fetuses with ossification delays and variations of ribs, concurrent with maternal toxicity at ≥640/160 mg/kg/day piperacillin and tazobactam (0.5 times and 1 times the human dose of piperacillin and tazobactam, respectively, based on body-surface area).

Peri/postnatal development in rats was impaired with reduced pup weights, increased stillbirths, and increased pup mortality concurrent with maternal toxicity after intraperitoneal administration of tazobactam alone at doses ≥320 mg/kg/day (2 times the human dose based on body surface area) or of the combination piperacillin and tazobactam at doses ≥640/160 mg/kg/day (0.5 times and 1 times the human dose of piperacillin and tazobactam, respectively, based on body-surface area) from gestation day 17 through lactation day 21.

8.2 Lactation

Risk Summary

Piperacillin is excreted in human milk; tazobactam concentrations in human milk have not been studied. No information is available on the effects of piperacillin and tazobactam on the breast- fed child or on milk production. The developmental and health benefits of breastfeeding should be considered along with the mother’s clinical need for Piperacillin and Tazobactam for Injection and Sodium Chloride Injection and any potential adverse effects on the breast-fed child from Piperacillin and Tazobactam for Injection and Sodium Chloride Injection or from the underlying maternal condition.

8.4 Pediatric Use

The safety and effectiveness of Piperacillin and Tazobactam for Injection and Sodium Chloride Injection for intra-abdominal infections, and nosocomial pneumonia have been established in pediatric patients 2 months of age and older.

Use of Piperacillin and Tazobactam for Injection and Sodium Chloride Injection in pediatric patients 2 months of age and older with intra-abdominal infections including appendicitis and/or peritonitis is supported by evidence from well-controlled studies and pharmacokinetic studies in adults and in pediatric patients. This includes a prospective, randomized, comparative, open-label clinical trial with 542 pediatric patients 2 to 12 years of age with intra-abdominal infections (including appendicitis (complicated by rupture or abscess) and/or peritonitis), in which 273 pediatric patients received piperacillin and tazobactam [see Adverse Reactions (6.1) and Clinical Pharmacology (12.3)].

Use of Piperacillin and Tazobactam for Injection and Sodium Chloride Injection in pediatric patients 2 months of age and older with nosocomial pneumonia is supported by evidence from well-controlled studies in adults with nosocomial pneumonia, a simulation study performed with a population pharmacokinetic model, and a retrospective, cohort study of pediatric patients with nosocomial pneumonia in which 140 pediatric patients were treated with Piperacillin and Tazobactam for Injection and 267 patients treated with comparators (which included ticarcillinclavulanate, carbapenems, ceftazidime, cefepime, or ciprofloxacin) [see Adverse Reactions (6.1) and Clinical Pharmacology (12.3)].

Because of the limitations of the available strengths and administration requirements (i.e., administration of fractional doses is not recommended) of Piperacillin and Tazobactam for Injection and Sodium Chloride Injection, and to avoid unintentional overdose, this product is not recommended for use if a dose of Piperacillin and Tazobactam for Injection and Sodium Chloride Injection, that does not equal 2.25 g, 3.375 g, or 4.5 g is required, and an alternative formulation of piperacillin and tazobactam for injection should be considered [see Dosage and Administration (2.5)].

The safety and effectiveness of Piperacillin and Tazobactam for Injection and Sodium Chloride Injection have not been established in pediatric patients less than 2 months of age [see Clinical Pharmacology (12) and Dosage and Administration (2)].

Dosage of Piperacillin and Tazobactam for Injection and Sodium Chloride Injection in pediatric patients with renal impairment has not been determined.

8.5 Geriatric Use

Patients over 65 years are not at an increased risk of developing adverse effects solely because of age. However, dosage should be adjusted in the presence of renal impairment [see Dosage and Administration (2)].

In general, dose selection for an elderly patient should be cautious, usually starting at the low end of the dosing range, reflecting the greater frequency of decreased hepatic, renal, or cardiac function, and of concomitant disease or other drug therapy.

Piperacillin and Tazobactam for Injection and Sodium Chloride Injection contains a total of 220 mg, 256 mg, 440 mg of sodium per 2.25 g, 3.375 g, and 4.5 g product, respectively. At the usual recommended doses, patients would receive between 1,320 and 1,760 mg/day of sodium. The geriatric population may respond with a blunted natriuresis to salt loading. This may be clinically important with regard to such diseases as congestive heart failure [see Warnings and Precautions (5.8)].

This drug is known to be substantially excreted by the kidney, and the risk of toxic reactions to this drug may be greater in patients with impaired renal function. Because elderly patients are more likely to have decreased renal function, care should be taken in dose selection, and it may be useful to monitor renal function [see Warnings and Precautions (5.7)].

8.6 Renal Impairment

In adult patients with creatinine clearance ≤ 40 mL/min and dialysis patients (hemodialysis and CAPD), the intravenous dose of Piperacillin and Tazobactam for Injection and Sodium Chloride Injection should be reduced to the degree of renal function impairment [see Dosage and Administration (2)].

8.7 Hepatic Impairment

Dosage adjustment of Piperacillin and Tazobactam for Injection and Sodium Chloride Injection is not warranted in patients with hepatic cirrhosis [see Clinical Pharmacology (12.3)].

8.8 Patients with Cystic Fibrosis

As with other semisynthetic penicillins, piperacillin therapy has been associated with an increased incidence of fever and rash in cystic fibrosis patients.

10 OVERDOSAGE

There have been postmarketing reports of overdose with piperacillin and tazobactam. The majority of those events experienced, including nausea, vomiting, and diarrhea, have also been reported with the usual recommended dosages. Patients may experience neuromuscular excitability or seizures if higher than recommended doses are given intravenously (particularly in the presence of renal failure) [see Warnings and Precautions (5.6)].

Treatment should be supportive and symptomatic according to the patient's clinical presentation. Excessive serum concentrations of either piperacillin or tazobactam may be reduced by hemodialysis. Following a single 3.375 g dose of piperacillin and tazobactam, the percentage of the piperacillin and tazobactam dose removed by hemodialysis was approximately 31% and 39%, respectively [see Clinical Pharmacology (12)].

11 DESCRIPTION

Piperacillin and Tazobactam for Injection and Sodium Chloride Injection is an injectable antibacterial combination product consisting of the semisynthetic antibacterial piperacillin sodium and the beta-lactamase inhibitor tazobactam sodium for intravenous administration.

Piperacillin sodium is derived from D(-)-α-aminobenzyl-penicillin. The chemical name of piperacillin sodium is sodium (2S,5R,6R)-6-[(R)-2-(4-ethyl-2,3-dioxo-1-piperazine-carboxamido)-2-phenylacetamido]-3,3-dimethyl-7-oxo-4-thia-1-azabicyclo[3.2.0]heptane-2-carboxylate. The chemical formula is C23H26N5NaO7S and the molecular weight is 539.5. The chemical structure of piperacillin sodium is:

Tazobactam sodium, a derivative of the penicillin nucleus, is a penicillanic acid sulfone. Its chemical name is sodium (2S,3S,5R)-3-methyl-7-oxo-3-(1H-1,2,3-triazol-1-ylmethyl)-4-thia-1-azabicyclo[3.2.0]heptane-2-carboxylate-4,4-dioxide. The chemical formula is C10H11N4NaO5S and the molecular weight is 322.3. The chemical structure of tazobactam sodium is:

Piperacillin and Tazobactam for Injection and Sodium Chloride Injection is supplied as a sterile powder for injection and a sterile solution in a single-dose DUPLEX® Container with a strength of 2.25 g, 3.375 g, or 4.5 g in the following presentations:

- 2.25 g: contains 2 grams of piperacillin (equivalent to 2.085 g of piperacillin sodium), 0.25 g of tazobactam (equivalent to 0.269 g of tazobactam sodium), 0.5 mg of edetate sodium dihydrate (EDTA), and 100 mg of sodium citrate dihydrate in the powder chamber. The diluent chamber contains 225 mg of sodium chloride and 50 mL of water for injection.
- 3.375 g: contains 3 grams of piperacillin (equivalent to 3.127 g of piperacillin sodium) and 0.375 g of tazobactam (equivalent to 0.402 g of tazobactam sodium), 0.75 mg of EDTA, and 150 mg of sodium citrate dihydrate in the powder chamber. The diluent chamber contains 150 mg of sodium chloride and 50 mL of water for injection.
- 4.5 g: contains 4 grams of piperacillin (equivalent to 4.170 g of piperacillin sodium), 0.5 g of tazobactam (equivalent to 0.538 g of tazobactam sodium), 1 mg of EDTA, and 200 mg of sodium citrate dihydrate. The diluent chamber contains 450 mg of sodium chloride and 100 mL of water for injection.

Piperacillin and Tazobactam for Injection and Sodium Chloride Injection contains a total of 9.6 mEq (220 mg), 11.1 mEq (256 mg), and 19.1 mEq (440 mg) of sodium (Na+) per 2.25 g, 3.375 g, and 4.5 g product, respectively [see Warnings and Precautions (5.8) and Use in Specific Populations (8.5)].

The reconstituted solution has a pH between 5.0 and 7.0. The osmolality of the reconstituted solution of Piperacillin and Tazobactam for Injection and Sodium Chloride Injection is approximately 318 mOsmol/kg for the 2.25 g strength, approximately 348 mOsmol/kg for the 3.375 g strength, and approximately 318 mOsmol/kg for the 4.5 g strength.

Piperacillin and Tazobactam for Injection and Sodium Chloride Injection Meets USP Monograph Organic Impurities Procedure 3.

The DUPLEX® Container is a flexible dual chamber container. After removing the peelable foil strip, activating the seals, and thoroughly mixing, the reconstituted drug product is hyperosmotic and is intended for single intravenous use. The product (diluent and drug) contact layer is a mixture of thermoplastic rubber and a polypropylene copolymer that contains no plasticizers.

Not made with natural rubber latex, PVC or Di(2-ethylhexyl)phthalate (DEHP).

12 CLINICAL PHARMACOLOGY

12.1 Mechanism of Action

Piperacillin and Tazobactam for Injection and Sodium Chloride Injection is an antibacterial drug [see Microbiology (12.4)].

12.2 Pharmacodynamics

The pharmacodynamic parameter for piperacillin and tazobactam that is most predictive of clinical and microbiological efficacy is time above MIC.

12.3 Pharmacokinetics

The mean and coefficients of variation (CV%) for the pharmacokinetic parameters of piperacillin and tazobactam after multiple intravenous doses are summarized in Table 6.

Table 6: Mean (CV%) Piperacillin and Tazobactam PK Parameters
Piperacillin
Piperacillin and Tazobactam Dose [Piperacillin and tazobactam were given in combination, infused over 30 minutes.] | Cmax (mcg/mL) | AUC [Numbers in []parentheses are coefficients of variation [CV%].] (mcg∙h/mL) | CL (mL/min) | V (L) | T1/2 (h) | CLR (mL/min)
2.25 g | 134 | 131 [14] | 257 | 17.4 | 0.79 | --
3.375 g | 242 | 242 [10] | 207 | 15.1 | 0.84 | 140
4.5 g | 298 | 322 [16] | 210 | 15.4 | 0.84 | --
Tazobactam
Piperacillin and Tazobactam Dose | Cmax (mcg/mL) | AUC (mcg∙h/mL) | CL (mL/min) | V (L) | T1/2 (h) | CLR (mL/min)
2.25 g | 15 | 16.0 [21] | 258 | 17.0 | 0.77 | --
3.375 g | 24 | 25.0 [8] | 251 | 14.8 | 0.68 | 166
4.5 g | 34 | 39.8 [15] | 206 | 14.7 | 0.82 | --
Cmax : maximum observed concentration, AUC: Area under the curve, CL=clearance, CLR= Renal clearance
V=volume of distribution, T1/2 = elimination half-life

Peak plasma concentrations of piperacillin and tazobactam are attained immediately after completion of an intravenous infusion of Piperacillin and Tazobactam for Injection and Sodium Chloride Injection. Piperacillin plasma concentrations, following a 30-minute infusion of Piperacillin and Tazobactam for Injection and Sodium Chloride Injection, were similar to those attained when equivalent doses of piperacillin were administered alone. Steady-state plasma concentrations of piperacillin and tazobactam were similar to those attained after the first dose due to the short half-lives of piperacillin and tazobactam.

Distribution

Both piperacillin and tazobactam are approximately 30% bound to plasma proteins. The protein binding of either piperacillin or tazobactam is unaffected by the presence of the other compound. Protein binding of the tazobactam metabolite is negligible.

Piperacillin and tazobactam are widely distributed into tissues and body fluids including intestinal mucosa, gallbladder, lung, female reproductive tissues (uterus, ovary, and fallopian tube), interstitial fluid, and bile. Mean tissue concentrations are generally 50% to 100% of those in plasma. Distribution of piperacillin and tazobactam into cerebrospinal fluid is low in subjects with non-inflamed meninges, as with other penicillins (see Table 7).

Table 7: Piperacillin and Tazobactam Concentrations in Selected Tissues and Fluids
after Single 4 g/0.5 g 30-min Intravenous Infusion of Piperacillin and Tazobactam
Tissue or Fluid | N [Each subject provided a single sample.] | Sampling period [Time from the start of the infusion] (h) | Mean PIP Concentration Range (mg/L) | Tissue:Plasma Range | Tazo Concentration Range (mg/L) | Tazo Tissue:Plasma Range
Skin | 35 | 0.5 – 4.5 | 34.8 – 94.2 | 0.60 – 1.1 | 4.0 – 7.7 | 0.49 – 0.93
Fatty Tissue | 37 | 0.5 – 4.5 | 4.0 – 10.1 | 0.097 – 0.115 | 0.7 – 1.5 | 0.10 – 0.13
Muscle | 36 | 0.5 – 4.5 | 9.4 – 23.3 | 0.29 – 0.18 | 1.4 – 2.7 | 0.18 – 0.30
Proximal Intestinal Mucosa | 7 | 1.5 – 2.5 | 31.4 | 0.55 | 10.3 | 1.15
Distal Intestinal Mucosa | 7 | 1.5 – 2.5 | 31.2 | 0.59 | 14.5 | 2.1
Appendix | 22 | 0.5 – 2.5 | 26.5 – 64.1 | 0.43 – 0.53 | 9.1 – 18.6 | 0.80 – 1.35

Elimination

Metabolism

Piperacillin is metabolized to a minor microbiologically active desethyl metabolite. Tazobactam is metabolized to a single metabolite that lacks pharmacological and antibacterial activities.

Excretion

Following single or multiple Piperacillin and Tazobactam for Injection and Sodium Chloride Injection doses to healthy subjects, the plasma half-life of piperacillin and of tazobactam ranged from 0.7 to 1.2 hours and was unaffected by dose or duration of infusion.

Both piperacillin and tazobactam are eliminated via the kidney by glomerular filtration and tubular secretion. Piperacillin is excreted rapidly as unchanged drug with 68% of the administered dose excreted in the urine. Tazobactam and its metabolite are eliminated primarily by renal excretion with 80% of the administered dose excreted as unchanged drug and the remainder as the single metabolite. Piperacillin, tazobactam and desethyl piperacillin are also secreted into the bile.

Specific Populations

Patients with Renal Impairment

After the administration of single doses of piperacillin and tazobactam to subjects with renal impairment, the half-life of piperacillin and of tazobactam increases with decreasing creatinine clearance. At creatinine clearance below 20 mL/min, the increase in half-life is twofold for piperacillin and fourfold for tazobactam compared to subjects with normal renal function. Dosage adjustments for Piperacillin and Tazobactam for Injection and Sodium Chloride Injection are recommended when creatinine clearance is below 40 mL/min in patients receiving the usual recommended daily dose of Piperacillin and Tazobactam for Injection and Sodium Chloride Injection. Specific recommendations for the treatment of adult patients with renal impairment are presented in another section of the prescribing information [see Dosage and Administration (2)].

Hemodialysis removes 30% to 40% of a piperacillin and tazobactam dose with an additional 5% of the tazobactam dose removed as the tazobactam metabolite. Peritoneal dialysis removes approximately 6% and 21% of the piperacillin and tazobactam doses, respectively, with up to 16% of the tazobactam dose removed as the tazobactam metabolite. Dosage recommendations for patients undergoing hemodialysis are presented in another section of the prescribing information [see Dosage and Administration (2)].

Patients with Hepatic Impairment

The half-life of piperacillin and of tazobactam increases by approximately 25% and 18%, respectively, in patients with hepatic cirrhosis compared to healthy subjects. However, this difference does not warrant dosage adjustment of Piperacillin and Tazobactam for Injection and Sodium Chloride Injection due to hepatic cirrhosis.

Pediatric Patients

Piperacillin and tazobactam pharmacokinetics were studied in pediatric patients 2 months of age and older. The clearance of both compounds is slower in the younger patients compared to older pediatric patients and adults.

In a population PK analysis, estimated clearance for 9 month-old to 12 year-old patients was comparable to adults, with a population mean (SE) value of 5.64 (0.34) mL/min/kg. The piperacillin clearance estimate is 80% of this value for pediatric patients 2 to 9 months old. In patients younger than 2 months of age, clearance of piperacillin is slower compared to older pediatric patients; however, it is not adequately characterized for dosing recommendations. The population mean (SE) for piperacillin volume of distribution is 0.243 (0.011) L/kg and is independent of age.

Geriatric Patients

The impact of age on the pharmacokinetics of piperacillin and tazobactam was evaluated in healthy male subjects, aged 18 to 35 years (n=6) and aged 65 to 80 years (n=12). Mean half-life for piperacillin and tazobactam was 32% and 55% higher, respectively, in the elderly compared to the younger subjects. This difference may be due to age-related changes in creatinine clearance.

Race

The effect of race on piperacillin and tazobactam was evaluated in healthy male volunteers. No difference in piperacillin or tazobactam pharmacokinetics was observed between Asian (n=9) and White (n=9) healthy volunteers who received single 4/0.5 g doses.

Drug Interactions

The potential for pharmacokinetic drug interactions between Piperacillin and Tazobactam for Injection and Sodium Chloride Injection and aminoglycosides, probenecid, vancomycin, heparin, vecuronium, and methotrexate has been evaluated [see Drug Interactions (7)].

12.4 Microbiology

Mechanism of Action

Piperacillin sodium exerts bactericidal activity by inhibiting septum formation and cell wall synthesis of susceptible bacteria. In vitro, piperacillin is active against a variety of gram-positive and gram-negative aerobic and anaerobic bacteria. Tazobactam sodium has little clinically relevant in vitro activity against bacteria due to its reduced affinity to penicillin-binding proteins. It is, however, a beta-lactamase inhibitor of the Molecular class A enzymes, including Richmond-Sykes class III (Bush class 2b & 2b') penicillinases and cephalosporinases. It varies in its ability to inhibit class II and IV (2a & 4) penicillinases. Tazobactam does not induce chromosomally-mediated beta-lactamases at tazobactam concentrations achieved with the recommended dosage regimen.

Antimicrobial Activity

Piperacillin and Tazobactam for Injection and Sodium Chloride Injection has been shown to be active against most isolates of the following microorganisms, both in vitro and in clinical infections [see Indications and Usage (1)]:

Aerobic bacteria
Gram-positive bacteria
Staphylococcus aureus (methicillin susceptible isolates only)

Gram-negative bacteria
Acinetobacter baumannii
Escherichia coli
Haemophilus influenzae (excluding beta-lactamase negative, ampicillin-resistant isolates)
Klebsiella pneumoniae
Pseudomonas aeruginosa (given in combination with an aminoglycoside to which the isolate is susceptible)

Anaerobic bacteria
Bacteroides fragilis group (B. fragilis, B. ovatus, B. thetaiotaomicron, and B. vulgatus)

The following in vitro data are available, but their clinical significance is unknown. At least 90 percent of the following bacteria exhibit an in vitro minimum inhibitory concentration (MIC) less than or equal to the susceptible breakpoint for piperacillin and tazobactam against isolates of similar genus or organism group. However, the efficacy of Piperacillin and Tazobactam for Injection and Sodium Chloride Injection in treating clinical infections caused by these bacteria has not been established in adequate and well-controlled clinical trials.

Aerobic bacteria
Gram-positive bacteria
Enterococcus faecalis (ampicillin or penicillin-susceptible isolates only)
Staphylococcus epidermidis (methicillin susceptible isolates only)
Streptococcus agalactiae [These are not beta-lactamase producing bacteria and, therefore, are susceptible to piperacillin alone.]
Streptococcus pneumoniae (penicillin-susceptible isolates only)
Streptococcus pyogenes
Viridans group streptococci

Gram-negative bacteria
Citrobacter koseri
Moraxella catarrhalis
Morganella morganii
Neisseria gonorrhoeae
Proteus mirabilis
Proteus vulgaris
Serratia marcescens
Providencia stuartii
Providencia rettgeri
Salmonella enterica

Anaerobic bacteria
Clostridium perfringens
Bacteroides distasonis
Prevotella melaninogenica

Susceptibility Testing

For specific information regarding susceptibility test interpretive criteria, and associated test methods and quality control standards recognized by FDA for this drug, please see: https://www.fda.gov/STIC.

13 NONCLINICAL TOXICOLOGY

13.1 Carcinogenesis, Mutagenesis, Impairment of Fertility

Carcinogenesis

Long-term carcinogenicity studies in animals have not been conducted with piperacillin and/or tazobactam.

Mutagenesis

Piperacillin and tazobactam were negative in microbial mutagenicity assays, the unscheduled DNA synthesis (UDS) test, a mammalian point mutation (Chinese hamster ovary cell HPRT) assay, and a mammalian cell (BALB/c-3T3) transformation assay. In vivo, piperacillin and tazobactam did not induce chromosomal aberrations in rats.

Fertility

Reproduction studies have been performed in rats and have revealed no evidence of impaired fertility when piperacillin and tazobactam is administered intravenously up to a dose of 1280/320 mg/kg piperacillin and tazobactam, which is similar to the maximum recommended human daily dose based on body-surface area (mg/m^2).

15 REFERENCES

1. Jensen J-US, Hein L, Lundgren B, et al. BMJ Open 2012; 2:e000635. doi:10.1136.

16 HOW SUPPLIED/STORAGE AND HANDLING

Piperacillin and Tazobactam for Injection USP and Sodium Chloride Injection USP is a white to off-white powder and a clear, colorless solution supplied in a single-dose DUPLEX® Container (packaged 24 single-dose units per case) in the following strengths described in Table 8 below:

Table 8: Strengths, Volume of Diluent, National Drug Code (NDC), Total Sodium for
Piperacillin and Tazobactam for Injection and Sodium Chloride Injection
Strength (piperacillin and tazobactam) | Piperacillin | Tazobactam | Volume of Diluent | NDC | Total Sodium | REF
2.25 g | 2 g | 0.25 g | 50 mL of 0.45% Sodium Chloride | 0264- 3446-11 | 9.6 mEq (220 mg) | 3446-11
3.375 g | 3 g | 0.375 g | 50 mL of 0.3% Sodium Chloride | 0264- 3448-11 | 11.1 mEq (256 mg) | 3448-11
4.5 g | 4 g | 0.5 g | 100 mL of 0.45% Sodium Chloride | 0264- 3450-22 | 19.1 mEq (440 mg) | 3450-22

Prior to reconstitution, store Piperacillin and Tazobactam for Injection USP and Sodium Chloride Injection USP at 20°C to 25°C (68°F to 77°F); excursions permitted to 15°C to 30°C (59°F to 86°F). [See USP Controlled Room Temperature.]

Do not remove the foil strip until ready to use to protect from light. After removal of the foil strip, product must be used within 7 days, but not beyond the labeled expiration date. Protect from light after removal of foil strip.

Storage conditions for reconstituted Piperacillin and Tazobactam for Injection are described in another section of labeling [see Dosage and Administration (2.5)].

Do not freeze.

17 PATIENT COUNSELING INFORMATION

Serious Hypersensitivity Reactions

Advise patients, their families, or caregivers that serious hypersensitivity reactions, including serious allergic cutaneous reactions, could occur with use of Piperacillin and Tazobactam for Injection and Sodium Chloride Injection that require immediate treatment. Ask them about any previous hypersensitivity reactions to Piperacillin and Tazobactam for Injection and Sodium Chloride Injection, other beta-lactams (including cephalosporins), or other allergens [see Warnings and Precautions (5.2)].

Hemophagocytic Lymphohistiocytosis

Prior to initiation of treatment with Piperacillin and Tazobactam for Injection and Sodium Chloride Injection, inform patients that excessive immune activation may occur with Piperacillin and Tazobactam for Injection and Sodium Chloride Injection and that they should report signs or symptoms such as fever, rash, or lymphadenopathy to a healthcare provider immediately [see Warnings and Precautions (5.3)].

High Sodium Load

Piperacillin and Tazobactam for Injection and Sodium Chloride Injection contains a high sodium load. Instruct patients to inform their healthcare provider if they develop symptoms of difficulty breathing, swelling, or increased weight [see Warnings and Precautions (5.8)].

Diarrhea

Advise patients, their families, or caregivers that diarrhea is a common problem caused by antibacterial drugs, including Piperacillin and Tazobactam for Injection and Sodium Chloride Injection, which usually ends when the drug is discontinued. Sometimes after starting treatment with antibacterial drugs, patients can develop watery and bloody stools (with or without stomach cramps and fever) even as late as two or more months after having taken the last dose of the drug. If this occurs, patients should contact their physician as soon as possible [see Warnings and Precautions (5.9)].

Antibacterial Resistance

Patients should be counseled that antibacterial drugs including Piperacillin and Tazobactam for Injection and Sodium Chloride Injection should only be used to treat bacterial infections. They do not treat viral infections (e.g., the common cold). When Piperacillin and Tazobactam for Injection and Sodium Chloride Injection is prescribed to treat a bacterial infection, patients should be told that although it is common to feel better early in the course of therapy, the medication should be taken exactly as directed. Skipping doses or not completing the full course of therapy may (1) decrease the effectiveness of the immediate treatment and (2) increase the likelihood that bacteria will develop resistance and will not be treatable by Piperacillin and Tazobactam for Injection and Sodium Chloride Injection or other antibacterial drugs in the future.

Pregnancy and Lactation

Patients should be counseled that Piperacillin and Tazobactam for Injection and Sodium Chloride Injection can cross the placenta in humans and is excreted in human milk [see Use in Specific Populations (8.1, 8.2)].

Manufactured for:
B. Braun Medical Inc.
Bethlehem, PA 18018-3524 USA
1-800-227-2862

Manufactured by:
ACS Dobfar S.p.A.
Prepared in Italy. API from Italy.

CLINITEST® is a registered trademark of Siemens Healthcare Diagnostics Inc.

DUPLEX® is a registered trademark of B. Braun Medical Inc.

Y36-003-102 LD-803-4

PRINCIPAL DISPLAY PANEL – 2.25 g Container

Piperacillin and Tazobactam
for Injection USP and
Sodium Chloride Injection USP

2.25 g*

50 mL

NDC 0264-3446-11
DUPLEX® CONTAINER

USE ONLY AFTER MIXING CONTENTS OF BOTH CHAMBERS.
FOR INTRAVENOUS INFUSION.
SINGLE-DOSE

* Each dry powder chamber provides 2 g piperacillin (equivalent to 2.085 g of
piperacillin sodium), 0.25 g tazobactam (equivalent to 0.268 g of tazobactam
sodium), 0.5 mg of edetate disodium dihydrate, and 100 mg of sodium citrate
dihydrate. Contains no preservative.

After reconstitution each 50 mL single-dose DUPLEX® unit contains Piperacillin and
Tazobactam for Injection (equivalent to 2 g of piperacillin and 0.25 g of tazobactam)
and 50 mL of 0.45% sodium chloride injection. Total sodium content of 220 mg (9.6
mEq). Approximate osmolality: 318 mOsmol/kg. Dosage: see Prescribing Information.

Prior to Reconstitution: Store at 20°C to 25°C (68°F to 77°F); excursions permitted
to 15°C to 30°C (59°F to 86°F). [See USP Controlled Room Temperature.] Use only if
container and seals are intact. Do not peel foil strip until ready for use in order to
protect from light. After foil strip removal, product must be used within 7 days, but
not beyond the labeled expiration date. Protect from light after removal of foil strip.

Reconstitute Prior to Administration: Hold container with set port in a downward
direction and fold the diluent chamber just below the solution meniscus. To activate
seal, squeeze folded diluent chamber until seal between diluent and drug chamber
opens, releasing diluent into drug chamber. Agitate the reconstituted solution until
the drug powder is completely dissolved. Fold the container a second time and
squeeze until seal between drug chamber and set port opens.

After Reconstitution: Use only if prepared solution is clear and free from particulate
matter. Use within 24 hours if stored at room temperature or within 7 days if stored
under refrigeration. Do not use in a series connection. Do not introduce additives into
this container. Prior to administration check for minute leaks by squeezing container
firmly. If leaks are found, discard container and solution as sterility may be impaired.
Do not freeze. Discard unused portion. Not made with natural rubber latex, PVC
or DEHP.

REF 3446-11

Rx only

Manufactured for:
B. Braun Medical Inc.

Exp :
Lot No:

NDC No. (01)10302643446113

Prepared in Italy. API from Italy.

Y37-002-612 LD-804-2

F50000403335

PRINCIPAL DISPLAY PANEL – 3.375 g Container

Piperacillin and Tazobactam
for Injection USP and
Sodium Chloride Injection USP

3.375 g*

50 mL

NDC 0264-3448-11
DUPLEX® CONTAINER

USE ONLY AFTER MIXING CONTENTS OF BOTH CHAMBERS.
FOR INTRAVENOUS INFUSION.
SINGLE-DOSE

* Each dry powder chamber provides 3 g piperacillin (equivalent to 3.127 g of
piperacillin sodium), 0.375 g tazobactam (equivalent to 0.402 g of tazobactam
sodium), 0.75 mg of edetate disodium dihydrate, and 150 mg of sodium citrate
dihydrate. Contains no preservative.

After reconstitution each 50 mL single-dose DUPLEX® unit contains Piperacillin and
Tazobactam for Injection (equivalent to 3 g of piperacillin and 0.375 g of tazobactam)
and 50 mL of 0.3% sodium chloride injection. Total sodium content of 256 mg (11.1
mEq). Approximate osmolality: 348 mOsmol/kg. Dosage: see Prescribing Information.

Prior to Reconstitution: Store at 20°C to 25°C (68°F to 77°F); excursions permitted
to 15°C to 30°C (59°F to 86°F). [See USP Controlled Room Temperature.] Use only if
container and seals are intact. Do not peel foil strip until ready for use in order to
protect from light. After foil strip removal, product must be used within 7 days, but
not beyond the labeled expiration date. Protect from light after removal of foil strip.

Reconstitute Prior to Administration: Hold container with set port in a downward
direction and fold the diluent chamber just below the solution meniscus. To activate
seal, squeeze folded diluent chamber until seal between diluent and drug chamber
opens, releasing diluent into drug chamber. Agitate the reconstituted solution until
the drug powder is completely dissolved. Fold the container a second time and
squeeze until seal between drug chamber and set port opens.

After Reconstitution: Use only if prepared solution is clear and free from particulate
matter. Use within 24 hours if stored at room temperature or within 7 days if stored
under refrigeration. Do not use in a series connection. Do not introduce additives into
this container. Prior to administration check for minute leaks by squeezing container
firmly. If leaks are found, discard container and solution as sterility may be impaired.
Do not freeze. Discard unused portion. Not made with natural rubber latex, PVC
or DEHP.

REF 3448-11

Rx only

Manufactured for:
B. Braun Medical Inc.

Exp :
Lot No:

NDC No. (01)10302643448117

Prepared in Italy. API from Italy.

Y37-002-613 LD-805-2

F50000403338

PRINCIPAL DISPLAY PANEL – 4.5 g Container

Piperacillin and Tazobactam
for Injection USP and
Sodium Chloride Injection USP

4.5 g*

100 mL

NDC 0264-3450-22
DUPLEX® CONTAINER

USE ONLY AFTER MIXING CONTENTS OF BOTH CHAMBERS.
FOR INTRAVENOUS INFUSION.
SINGLE-DOSE

* Each dry powder chamber provides 4 g piperacillin (equivalent to 4.170 g of
piperacillin sodium), 0.5 g tazobactam (equivalent to 0.537 g of tazobactam
sodium), 1 mg of edetate disodium dihydrate, and 200 mg of sodium citrate
dihydrate. Contains no preservative.

After reconstitution each 100 mL single-dose DUPLEX® unit contains Piperacillin and
Tazobactam for Injection (equivalent to 4 g of piperacillin and 0.5 g of tazobactam)
and 100 mL of 0.45% sodium chloride injection. Total sodium content of 440 mg (19.1
mEq). Approximate osmolality: 318 mOsmol/kg. Dosage: see Prescribing Information.

Prior to Reconstitution: Store at 20°C to 25°C (68°F to 77°F); excursions permitted
to 15°C to 30°C (59°F to 86°F). [See USP Controlled Room Temperature.] Use only if
container and seals are intact. Do not peel foil strip until ready for use in order to
protect from light. After foil strip removal, product must be used within 7 days, but
not beyond the labeled expiration date. Protect from light after removal of foil strip.

Reconstitute Prior to Administration: Hold container with set port in a downward
direction and fold the diluent chamber just below the solution meniscus. To activate
seal, squeeze folded diluent chamber until seal between diluent and drug chamber
opens, releasing diluent into drug chamber. Agitate the reconstituted solution until
the drug powder is completely dissolved. Fold the container a second time and
squeeze until seal between drug chamber and set port opens.

After Reconstitution: Use only if prepared solution is clear and free from particulate
matter. Use within 24 hours if stored at room temperature or within 7 days if stored
under refrigeration. Do not use in a series connection. Do not introduce additives into
this container. Prior to administration check for minute leaks by squeezing container
firmly. If leaks are found, discard container and solution as sterility may be impaired.
Do not freeze. Discard unused portion. Not made with natural rubber latex, PVC
or DEHP.

REF 3450-22

Rx only

Manufactured for:
B. Braun Medical Inc.

Exp :
Lot No:

NDC No. (01)10302643450226

Prepared in Italy. API from Italy.

Y37-002-614 LD-806-2

F50000403339